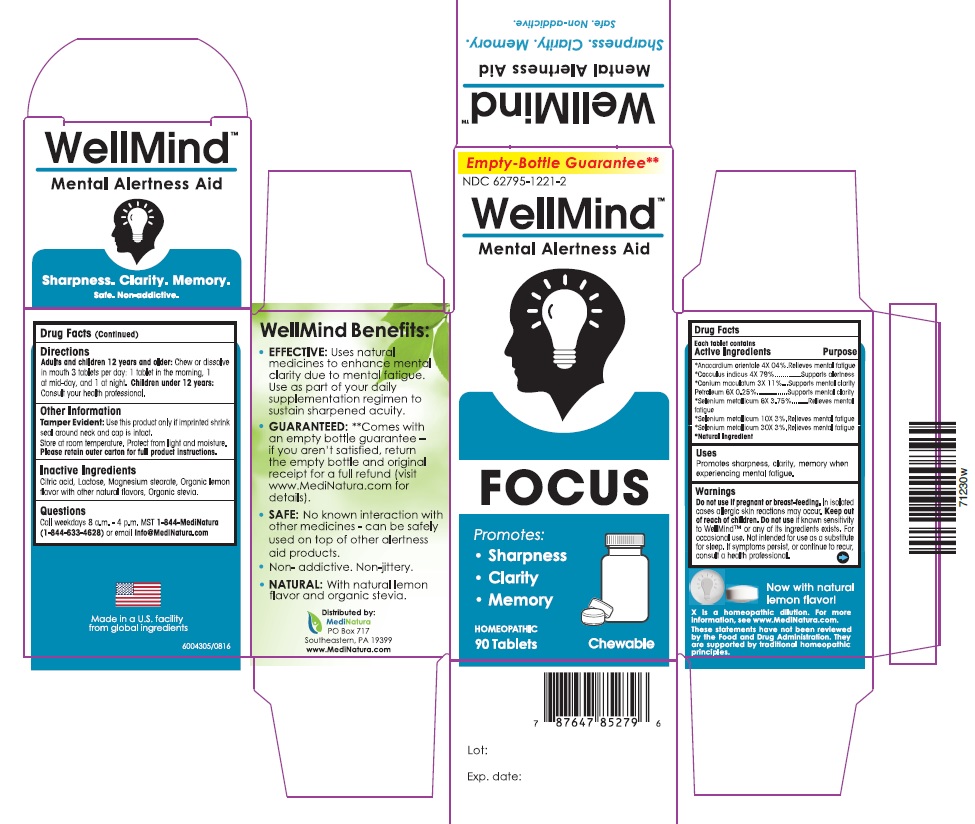 DRUG LABEL: WellMind Mental Focus
NDC: 62795-1221 | Form: TABLET
Manufacturer: MediNatura Inc.
Category: homeopathic | Type: HUMAN OTC DRUG LABEL
Date: 20220719

ACTIVE INGREDIENTS: SEMECARPUS ANACARDIUM JUICE 6 [hp_X]/1 1; ANAMIRTA COCCULUS SEED 4 [hp_X]/1 1; CONIUM MACULATUM FLOWERING TOP 3 [hp_X]/1 1; KEROSENE 6 [hp_X]/1 1; SELENIUM 6 [hp_X]/1 1
INACTIVE INGREDIENTS: STEVIA REBAUDIUNA LEAF; LACTOSE; MAGNESIUM STEARATE; CITRIC ACID ACETATE

WellMind Mental Focus

KEEP OUT OF REACH OF CHILDREN

Uses

Helps restore Mental Focus and Mental Clarity due to fatigue.

WARNINGS

Do not use if pregnant or breast-feeding. In isolated cases, allergic skin reactions may occur. Keep out of reach of children. Do not use if known sensitivity to WellMind TM or any of its ingredients exists. For occasional use. Not intended for use as a substitute for sleep. If symptoms persist, or continue to recur, consult a health professional.

DIRECTIONS

At first sign of symptoms:

Adults and children 12 years and older:

1 tablet every ½ to 1 hour until symptoms lessen, then continue with standard dosage. Do not exceed12 tablets in 24 hours.

For children under 12 years, consultyour health professional.

Standard Dosage:

Adults and children 12 years and older:

3 tablets per day, taking 1 tablet every 4 to 6 hours.

For children under 12 years, consult your health professional.

Allow tablets to dissolve completely in the mouth, do not swallow.

Purpose

Retores:

- Alertness
- Mental Clarity

ACTIVE INGREDIENTS

Acive Ingredients Purpose

*Anacardium orientale 6X.......................Relieves mental fatigue

*Cocculus indicus 4X..............................Supports alertness

*Conium maculatum 3X.........................Supports mental clarity

Petroleum 8X.........................................Supports mental clarity

*Selenium metallicum 6X, 12X, 30X.......Relieves mental fatigue

*Natural Ingredients

INACTIVE INGREDIENTS

Lactose, Magnesium stearate